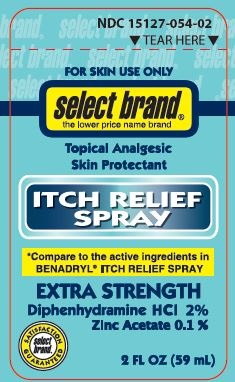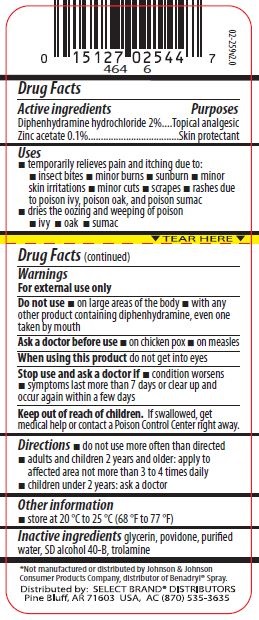 DRUG LABEL: Select Brand Itch Relief
NDC: 15127-054 | Form: SPRAY
Manufacturer: Select Brand
Category: otc | Type: HUMAN OTC DRUG LABEL
Date: 20150103

ACTIVE INGREDIENTS: DIPHENHYDRAMINE HYDROCHLORIDE .2 g/10 mL; ZINC ACETATE .01 g/10 mL
INACTIVE INGREDIENTS: ALCOHOL; GLYCERIN; POVIDONES; WATER; TROLAMINE

Select Brand Itch Relief Spray

Drug Facts

ACTIVE INGREDIENT

Active ingredients | Purpose
Diphenhydramine hydrochloride 2% | Topical analgesic
Zinc acetate 0.1% | Skin protectant

Uses

- temporarily relieves pain and itching due to:
  - insect bites
  - minor burns
  - sunburn
  - minor skin irritations
  - minor cuts
  - scrapes
  - rashes due to poison ivy, poison oak, and poison sumac
- dries the oozing and weeping of poison • ivy • oak • sumac

Warnings

For external use only.

Do not use

- on large areas of the body
- with any other product containing diphenhydramine, even one taken by mouth

Ask a doctor before use

- on chicken pox
- on measles

When using this product do not get into eyes

Stop use and ask a doctor if

- condition worsens
- symptoms last more than 7 days or clear up and occur again within a few days

Keep out of reach of children. If swallowed, get medical help or contact a Poison Control Center right away.

Directions

- do not use more than directed
- adults and children 2 years of age and older: spray on affected area not more than 3 to 4 times daily
- children under 2 years of age: ask a doctor

Other Information

- store at 20° C to 25° C (68° F to 77° F)

Inactive ingredients

glycerin, povidone, purified water, SD alcohol 40-B, trolamine

Distributed by:
SELECT BRAND DISTRIBUTORS

Pine Bluff, AR 71603 USA, AC(870) 535-3635

PRINCIPAL DISPLAY PANEL

FOR SKIN USE ONLY

select brand

Topical Analgesic

Skin Protectant

ITCH RELIEF SPRAY

*Compare to the active ingredients in

BENADRYL ITCH RELIEF SPRAY

EXTRA STRENGTH

Diphenhydramine HCl 2%

Zinc Acetate 0.1%

2 FL OZ (59 mL)